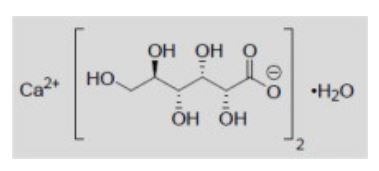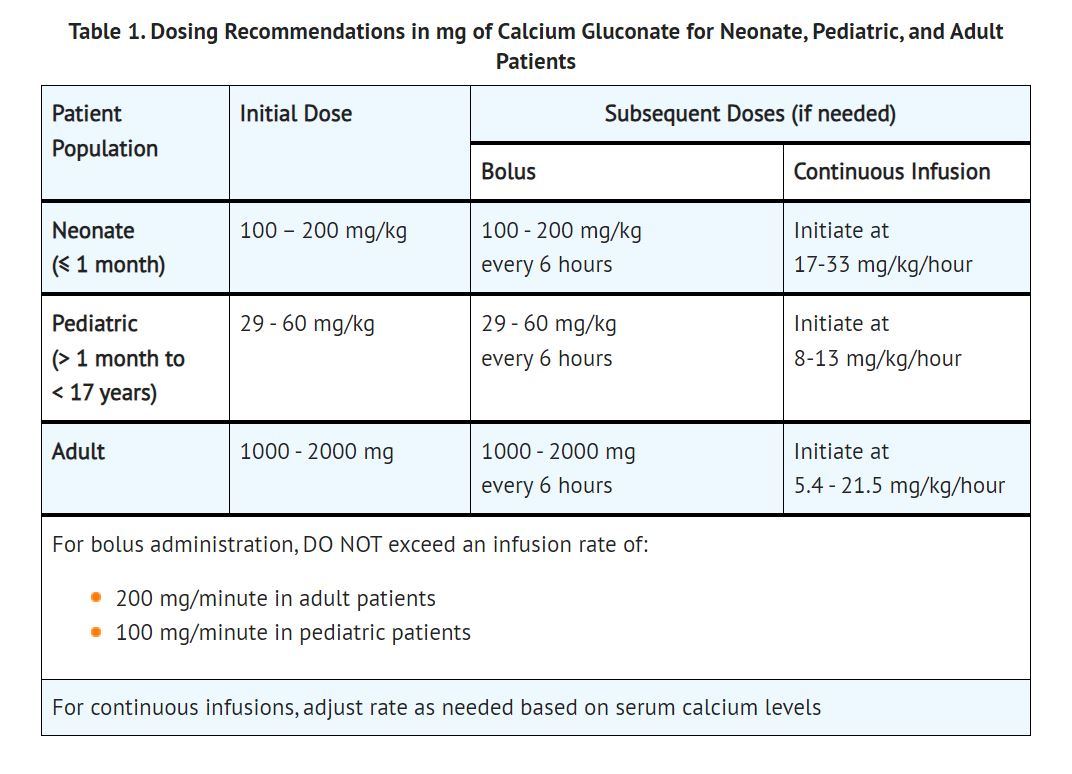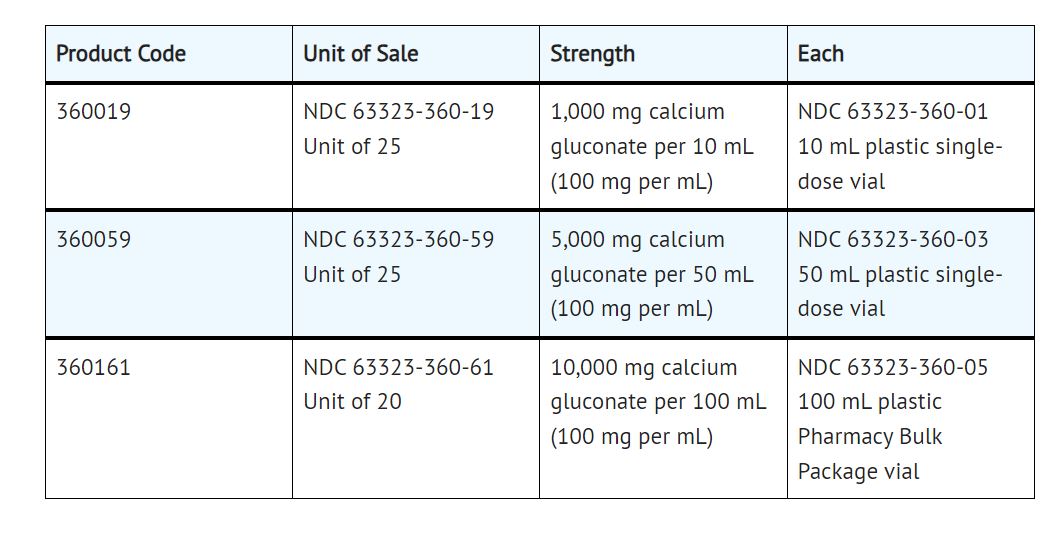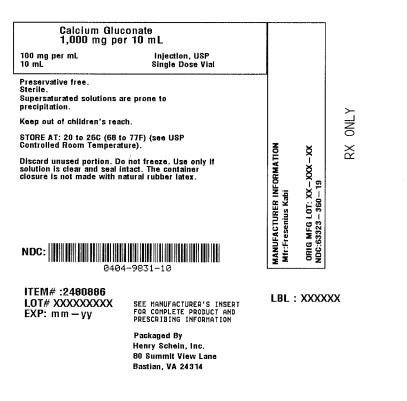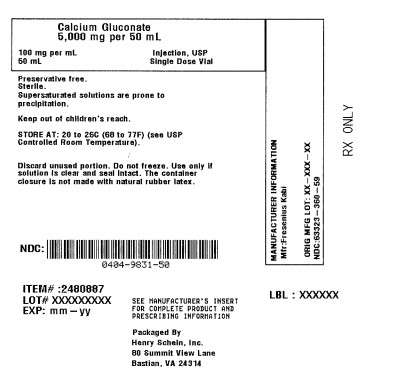 DRUG LABEL: Calcium Gluconate
NDC: 0404-9831 | Form: INJECTION, SOLUTION
Manufacturer: Henry Schein, Inc.
Category: prescription | Type: HUMAN PRESCRIPTION DRUG LABEL
Date: 20251103

ACTIVE INGREDIENTS: CALCIUM GLUCONATE MONOHYDRATE 98 mg/1 mL
INACTIVE INGREDIENTS: CALCIUM SACCHARATE; HYDROCHLORIC ACID; SODIUM HYDROXIDE

HIGHLIGHTS OF PRESCRIBING INFORMATION

These highlights do not include all the information needed to use CALCIUM GLUCONATE INJECTION safely and effectively. See full prescribing information for CALCIUM GLUCONATE INJECTION.
CALCIUM GLUCONATE injection, for intravenous use
Initial U.S. Approval: 1941

1 INDICATIONS AND USAGE

- Calcium Gluconate Injection is a form of calcium indicated for pediatric and adult patients for the treatment of acute symptomatic hypocalcemia. (1)
- Limitations of Use: The safety of Calcium Gluconate Injection for long term use has not been established. (1)

2 DOSAGE AND ADMINISTRATION

- Contains 100 mg of calcium gluconate per mL which contains 9.3 mg (0.465 mEq) of elemental calcium (2.1)
- Administer intravenously (bolus or continuous infusion) via a secure intravenous line (2.1)
- See Full Prescribing Information (FPI) for dilution instructions, administration rates, and appropriate monitoring (2.1)
- Individualize the dose within the recommended range in adults and pediatrics patients depending on the severity of symptoms of hypocalcemia the serum calcium level, and the acuity of onset of hypocalcemia. See Table 1 in the FPI for dosing recommendations in mg of calcium gluconate for neonates, pediatric and adult patients. (2.2)
- Measure serum calcium during intermittent infusions every 4 to 6 hours and during continuous infusion every 1 to 4 hours. (2.3)
- Calcium Gluconate Injection is not physically compatible with fluids containing phosphate or bicarbonate. Precipitation may result if mixed. See FPI for all drug incompatibilities. (2.5)
- Supplied in a single-dose vial or pharmacy bulk package (PBP). For PBP, dispense single doses to many patients in a pharmacy admixture program; use within 4 hours of puncture. (2.6)

3 DOSAGE FORMS AND STRENGTHS

Calcium Gluconate Injection, USP: (3)

- Single-dose vial: 1,000 mg per 10 mL (100 mg per mL)
- Single-dose vial: 5,000 mg per 50 mL (100 mg per mL)
- Pharmacy bulk package: 10,000 mg per 100 mL (100 mg per mL)

4 CONTRAINDICATIONS

- Hypercalcemia (4)
- Neonates (28 days of age or younger) receiving ceftriaxone (4)

5 WARNINGS AND PRECAUTIONS

- Arrhythmias with Concomitant Cardiac Glycoside Use: If concomitant therapy is necessary, Calcium Gluconate Injection should be given slowly in small amounts and close ECG monitoring is recommended (5.1)
- End-Organ Damage due to Intravascular Ceftriaxone-Calcium Precipitates: Concurrent use of intravenous ceftriaxone may cause life-threatening precipitates. Cases of fatal outcomes in neonates have occurred. (4, 5.2)
- Tissue Necrosis and Calcinosis: Calcinosis cutis can occur with or without extravasation of Calcium Gluconate Injection. Tissue necrosis, ulceration, and secondary infection are the most serious complications. If extravasation occurs or clinical manifestations of calcinosis cutis are noted, immediately discontinue intravenous administration at that site and treat as needed. (5.3)
- Hypotension, Bradycardia, and Cardiac Arrhythmias with Rapid Administration: To avoid adverse reactions that may follow rapid intravenous administration, Calcium Gluconate Injection should be diluted with 5% dextrose or normal saline and infused slowly, with careful ECG monitoring for cardiac arrhythmias. (5.4)
- Aluminum Toxicity: This product contains aluminum, up to 512 mcg per liter, that may be toxic. (5.5)

6 ADVERSE REACTIONS

The most common adverse events with Calcium Gluconate Injection are local soft tissue inflammation and necrosis, calcinosis cutis and calcification that are related to extravasation. Other adverse events include vasodilation, decreased blood pressure, bradycardia, cardiac arrhythmia, syncope, and cardiac arrest. (6)

To report SUSPECTED ADVERSE REACTIONS, contact Fresenius Kabi USA, LLC at 1-800-551-7176 or FDA at 1-800-FDA-1088 or www.fda.gov/medwatch.

7 DRUG INTERACTIONS

- Cardiac Glycoside: Synergistic arrhythmias may occur if calcium and cardiac glycosides are administered together. (7.1)
- Calcium Channel Blockers: Administration of calcium may reduce the response. (7.2)
- Drugs that may cause hypercalcemia: Vitamin D, vitamin A, thiazide diuretics, estrogen, calcipotriene and teriparatide administration may cause hypercalcemia. Monitor plasma calcium concentrations in patients taking these drugs concurrently. (7.3)

8 USE IN SPECIFIC POPULATIONS

- Geriatric use: Dosing in elderly patietns should be cautions, usually starting at the low end of the dosage range. (8.5)
- Renal impairment: Initiate with the lower limit of the dosage range and monitor serum calcium levels every 4 hours. (8.6, 2.4)

See 17 for PATIENT COUNSELING INFORMATION

Revised: 6/2023

FULL PRESCRIBING INFORMATION

1 INDICATIONS AND USAGE

Calcium Gluconate Injection is indicationd for pediatric and adult patients for the treatment of acute symptomatic hypocalcemia.

Limitations of Use

The safety of Calcium Gluconate Injection for long term use has not been established.

2 DOSAGE AND ADMINISTRATION

2.1 Important Administration Instructions

- Calcium Gluconate Injection contains 100 mg of calcium gluconate per mL which contains 9.3 mg (i.e., 0.465 mEq) of elemental calcium.
- Dilute Calcium Gluconate Injection prior to use in 5% dextrose or normal saline and assess for potential drug or IV fluid incompatibilities [see Dosage and Administration (2.5)].
- Inspect Calcium Gluconate Injection visually prior to administration. The solution should appear clear and colorless to slightly yellow. Do not administer if there is particulate matter or discoloration.
- Use the diluted solution immediately after preparation.
- Administer Calcium Gluconate Injection intravenously via a secure intravenous line to avoid calcinosis cutis and tissue necrosis [see Warnings and Precautions (5.3)].
- Administer Calcium Gluconate Injection by bolus administration nor continuous infusion:

For bolus intravenous administration:

- Dilute the dose [see Dosage and Administration (2.2)] of Calcium Gluconate Injection in 5% dextrose or normal saline to a concentration 10-50 mg/mL prior to administration. Administer the dose slowly and DO NOT exceed an infustion rate of 200 mg/minute in adults or 100 mg/minute in pediatric patients, including neonates. Monitor patients, vitals and electrocardiograph (ECG) during administration [see Warnings and Precautions (5.4)].

For continuous intravenous infusion:

- Dilute Calcium Gluconate Injection in 5% dextrose or normal saline to a concentration of 5.8-10 mg/mL prior to administration. Administer at the rate recommended in Table 1 [see Dosage and Administration (2.2)] and monitor patients, vitals, calcium and ECG during the infusion [see Warnings and Precautions (5.4)].
- Calcium Gluconate Injection is supplied in single-dose vials and pharmacy bulk packages [see Dosage and Administration (2.6)].

2.2 Recommended Dosage

Individualize the dose of Calcium Gluconate Injection within the recommended range depending on the severity of symptoms of hypocalcemia, the serum clacium level, and the acuity of onset of hypocalcemia.

Table 1 provides dosing recommendations for Calcium Gluconate Injection in mg of calcium gluconate for neonates, pediatric and adult patients.

2.3 Serum Calcium Monitoring

Measure serum calcium every 4 to 6 hours during intermittent infusions with Calcium Gluconate Injection and measure serum calcium every 1 to 4 hours during continuous infusion.

2.4 Dosage in Renal Impairment

For patients with renal impairment, initiate Calcium Gluconate Injection at the lowest dose of the recommended dose ranges for all age groups and monitor serum calcium levels every 4 hours.

2.5 Drug Incompatibilities

- Do not mix Calcium Gluconate Injection with ceftriaxone. Concurrent use of intravenous ceftriaxone and Calcium Gluconate Injection can lead to the formation of ceftriaxone-calcium precipitates. Concomitant use of ceftriaxone and intravenous calcium-containing products is contraindicated in neonates (28 days of age or younger) see Contraindications (4)]. In patients older than 28 days of age, ceftriaxone and calcium-containing products may be administered sequentially, provided the infusion lines are thoroughly flushed between infusions with a compatible fluid. Ceftriaxone must not be administered simultaneously with intravenous calcium-containing solutions via a Y-site in any age group [see Warnings and Precautions (5.2), Drug Interactions (7.3)].
- Do not mix Calcium Gluconate Injection with fluids containing bicarbonate or phosphate. Calcium Gluconate Injection is not physically compatible with fluids containing phosphate or bicarbonate. Precipitation may result if mixed.
- Do not mix Calcium Gluconate Injection with minocycline injection. Calcium complexes minocycline rendering it inactive.

2.6 Preparation of Pharmacy Bulk Package

The pharmacy bulk package (PBP) of Calcium Gluconate Injection is intended for dispensing of single doses to multiple patients in a pharmacy admixture program. Penetrate the container closure only one time with a suitable sterile transfer device or dispensing set that allows measured dispensing of the contents. Use the PBP only in a suitable ISO Class 5 work area such as a laminar flow hood (or an equivalent clean air compounding area). Complete dispensing from the pharmacy bulk vial within 4 hours after the container closure is penetrated. Each dose dispensed from the Pharmacy Bulk Package vial must be used immediately.

3 DOSAGE FORMS AND STRENGTHS

Calcium Gluconate Injection, USP is a clear, colorless to slightly yellow, solution avaialbe in the following:

- Single-dose vial: 1,000 mg per 10 mL (100 mg per mL)
- Single-dose vial: 5,000 mg per 50 mL (100 mg per mL)
- Pharmacy bulk package: 10,000 mg per 10 mL (100 mg per mL)

Each mL of Calcium Gluconate Injection, USP contains 9.3 mg (0.465 mEq) of elemental calcium.

4 CONTRAINDICATIONS

Calcium Gluconate Injection is contraindicated in:

- Hypercalcemia
- Neonates (28 days of age or younger) receiving ceftriaxone [see Warnings and Precautions (5.2)]

5 WARNINGS AND PRECAUTIONS

5.1 Arrhythmias with Concomitant Cardiac Glycoside Use

Cardiac arrhythmias may occur if calcium and cardiac glycosides are administered together. Hyperclacemia increases the risk of digoxin toxicity. Adminsitration of Calcium Gluconate Injection should be avoided in patients receiving cardiac glycosides. If concomitant therapy is necessary, Calcium Gluconate Injection should be given slowly in small amounts and with close ECG monitoring [see Drug Interactions (7.1)].

5.2 End-Organ Damage due to Intravascular Ceftriaxone-Calcium Precipitates

Concomitant use of ceftriaxone and Calcium Gluconate Injection is contraindicated in neonates (28 days of ane or younger) due to cases of fatal outcomes in neonates in which a crystalline material was observed in the lungs and kidneys at autopsy after ceftriaxone and calcium were administrated simultaneously through the same intravenous line. Concomitant administration can lead to the formation of ceftriaxone-calcium precipitates that may act as emboli, resulting in vascular spasm or infarction [see Contraindications (4)].

In patients older than 28 days of age, ceftriaxone and Calcium Gluconate Injection may be administered sequentially, provided the infusion lines are thoroughly flushed between infusions with a compatible fluid. Do not administer Ceftriaxone simultaneously with Calcium Gluconate Injection via a Y-site in any age group.

5.3 Tissue Necrosis and Calcinosis

Intravenous administration of Calcium Gluconate Injection and local trauma may result in calcinosis cutis due to transient increase in local calcium concentration. Calcinosis cutis can occur with or without extravasation of Calcium Gluconate Injection, is characterized by abnormal dermal deposits of calcium salts, and clinically manifests as papules, plaques, or nodules that may be associated with erythema, sweling, or induration. Tissue necrosis, ulceration, and secondary infection are the most serious complications.

If extravasation occurs or clinical manifestations of calcinosis cutis are noted, immediately discontinue intravenous administration at that site and treat as needed.

5.4 Hypotension, Bradycardia, and Cardiac Arrhythmias with Rapid Administration

Rapid injection of Calcium Gluconate Injection may cause vasodilation, decreased blood pressure, bradycardia, cardiac arrhythmias, syncope and cardiac arrest. To avoid adverse reactions that may follow rapid intravenous administration, Calcium Gluconate Injection should be diluted with 5% dextrose or normal saline and infused slowly. If rapid intravenous bolus of Calcium Gluconate Injection is required, the rate of intravenous administration should not exceed 200 mg/minute in adults and 100 mg/minute in pediatric patients and ECG monitoring during administration is recommended [see Dosage and Administration(2.1)].

5.5 Aluminum Toxicity

Calcium Gluconate Injection contains contains aluminum, up to 512 mcg per liter, that may be toxic. Aluminum may reach toxic levels with prolonged parenteral administration if kidney function is impaired. Premature neonates are particularly at risk because their kidneys are immature, and they require large amounts of calcium and phosphate solutions, which contain aluminum. Research indicates that patients with impaired kidney function, including premature neonates, who receive parenteral levels of aluminum at greater than 4 mcg/kg/day to 5 mcg/kg/day accumulate aluminum levels associated with central nervous system and bone toxicity. Tissue loading may occur at even lower rates of administration.

6 ADVERSE REACTIONS

The following serious adverse reactions are also described elsewhere in the labeling:

- Arrhythmias with Concomitant Cardiac Glycoside Use [see Warnings and Precautions (5.1)]
- End-Organ Damage due to Intravascular Ceftriaxone-Calcium Precipitates [see Warnings and Precautions (5.2)]
- Tissue Necrosis and Calcinosis [see Warnings and Precautions (5.3)]
- Hypotension, Bradycardia, and Cardiac Arrhythmias [see Warnings and Precautions (5.4)]
- Aluminum toxicity [see Warnings and precautions (5.5)]

The following adverse reactions associated with the use of calcium gluconate were identified in the literature. Because these reactions are reported voluntarily from a population of uncertain size, it is not always possible to estimate their frequency reliably or to establish a causal relationship to drug exposure.

Cardiovascular: Vasodilation, decreased blood pressure, bradycardia, cardiac arrhythmia, syncope, cardiac arrest

Administration site reactions:Local soft tissue inflammation, local necrosis, calcinosis cutis and calcification due to extravasation

7 DRUG INTERACTIONS

7.1 Cardiac Glycosides

Hypercalcemia increases the risk of digoxin toxicity, while digoxin may be therapeutically ineffective in the presence of hypocalcemia. Synergistic arrhythmias may occur if calcium and cardiac glycosides are administered together. Avoid administration of Calcium Gluconate Injection in patients receiving cardiac glycosides; if considered necessary, administer Calcium Gluconate injection slowly in small amounts and monitor ECG closely during administration.

7.2 Calcium Channel Blockers

Administration of calcium may reduce the response to calcium channel blockers.

7.3 Drugs that may cause Hypercalcemia

Vitamin D, vitamin A, thiazide diuretics, estrogen, calcipotriene and teriparatide administration may cause hypercalcemia. Monitor plasma calcium concentrations in patients taking these drugs concurrently.

8 USE IN SPECIFIC POPULATIONS

8.1 Pregnancy

Risk summary

Limited available data with Calcium Gluconate Injection use in pregnant women are insufficient to inform a drug associated risk of adverse developmental outcomes. There are risks to the mother and the fetus associated with hypocalcemia in pregnancy [see Clinical Considerations].

The estimated background risk of major birth defects and miscarriage for the indicated population is unknown. In the U.S. general population, the estimated background risk of major birth defects and miscarriage in clinically recognized pregnancies is 2-4% and 15-20%, respectively.

Clinical Considerations

Disease-associated maternal risk

Maternal hypocalcemia can result in an increased rate of spontaneous abortion, premature and dysfunctional labor, and possibly preeclampsia.

Fetal/Neonatal adverse reactions

Infants born to mothers with hypocalcemia can have associated fetal and neonatal hyperparathyroidism, which in turn can cause fetal and neonatal skeletal demineralization, subperiosteal bone resorption, osteitis fibrosa cystica and neonatal seizures. Infants born to mothers with hypocalcemia should be carefully monitored for signs of hypocalcemia or hypercalcemia, including neuromuscular irritability, apnea, cyanosis and cardiac rhythm disorders.

8.2 Lactation

Risk summary

Calcium is present in human milk as a natural component of human milk. It is not known whether intravenous administration of Calcium Gluconate Injection can alter calcium concentration in human milk. There are no data on the effects of Calcium Gluconate Injection on the breastfed infant, or on milk production. The developmental and health benefits of breastfeeding should be considered along with the mother's clinical need for Calcium Gluconate Injection and any potential adverse effects on the breastfed child from Calcium Gluconate Injection or from the underlying maternal condition.

8.4 Pediatric Use

The safety and effectiveness of Calcium Gluconate Injection have been established in pediatric patients for the treatment of acute, symptomatic hypocalcemia.

Pediatric approval for Calcium Gluconate Injection, including doses, is not based on adequate and well-controlled clinical studies. Safety and dosing recommendations in pediatric patients are based on published literature and clinical experience [see Dosage and Administration (2.2).

Concomitant use of ceftriaxone and Calcium Gluconate Injection is contraindicated in neonates (28 days of age or younger) due to reports of fatal outcomes associated with the presence of lung and kidney ceftriaxone-calcium precitpiates. In patients older than 28 days of age, ceftriaxone and Calcium Gluconate Injection may be administered sequentially, provided the infusion lines are thoroughly flushed between infusions with a compatible fluid [see Contraindications (4) and Warnings and Precautions (5.2)]. This product contains up to512 mcg/mL aluminum which may be toxic, particularly for premature neonates due to immature renal function. Parenteral administration of aluminum greater than 4 to 5 mcg/kg/day is associated with central nervous system and bone toxicity [see Warnings and Precautions (5.5)].

8.5 Geriatric Use

In general dose selection for an elderly patient should start at the lowest dose of the recommended dose range, reflecting the greater frequency of decreased hepatic, renal, or cardiac function, and of concomitant disease or oether drug therapy.

8.6 Renal Impairment

For patients with renal impairment, initiate Calcium Gluconate Injection at the loest dose of the recommended dose ranges across all age groups. Monitor serum calcium levels every 4 hours [see Dosage and Administration (2.4)].

8.7 Hepatic Impairment

Hepatic function does not impact the availability of ionized calcium after clacium gluconate intravenous administration. Dose adjustment in hepatically imapired patients may not be necessary.

10 OVERDOSAGE

Overdosage of Calcium Gluconate Injection may result in hypercalcemia. Symptoms of hypercalcemia typically develop when the total serum calcium concentration is ≥12 mg/dL. Neurologic symptoms include depression, weakness, fatigue, and confusion at lower levels, with patients experiencing hallucinations, disorientation, hypotonicity, seizures, and coma. Effects on the kidney include diminished ability to concentrate urine and diuresis.

If overdose of Calcium Gluconate Injection occurs immediately discontinue administration and provide supportive treatments to restore intravascular volume as well as promote calcium excretion in the urine if necessary.

11 DESCRIPTION

Calcium Gluconate Injection, USP is a sterile, preservative-free, nonpyrogenic, supersaturated solution of calcium gluconate, a form of calcium, for intravenous use.

Calcium Gluconate is calcium D-gluconate (1:2) monohydrate. The structural formula is:

Molecular formula: C12H22CaO14• H2O
Molecular weight: 448.39
Solubility in water: 3.5 g/100 mL at 25°C

Calcium Gluconate Injection, USP is available as 1,000 mg per 10 mL (100 mg per mL) or 5,000 mg per 50 mL (100 mg per mL) in a single-dose vial, or 10,000 mg per 100 mL (100 mg per mL) in a pharmacy bulk package.

Each mL of Calcium Gluconate Injection, USP contains 100 mg of calcium gluconate (equivalent to 94 mg of calcium gluconate and 4.5 mg of calcium saccharate tetrahydrate), hydrochloric acid and/or sodium hydroxide for pH adjustment (6.0 to 8.2) and sterile water for injection, q.s. It contains no antimicrobial agent.

Each mL of Calcium Gluconate Injection, USP contains 9.3 mg (0.465 mEq) of elemental calcium.

12 CLINICAL PHARMACOLOGY

12.1 Mechanism of Action

Intravenous administration of calcium gluconate increases serum ionized calcium level. Calcium gluconate dissociates into ionized calcium in plasma. Ionized calcium and gluconate are normal constituents of body fluids.

12.3 Pharmacokinetics

Absorption

Calcium Gluconate Injection is 100% bioavailable following intravenous injection.

Metabolism

Calcium iteself does not undergo direct metabolism. The release of ionized calcium from intravenous administration of calcium gluconate is direct and does not seem to be affected by the first pass through the liver.

Distribution

Calcium in the body is distributed mainly in skeleton (99%). Only 1% of the total body calcium is distributed within the extracellular fluids and soft tissues. About 50% of total serum calcium is in the ionized form and represents the biologically active part. 8% to 10% serum calcium is bound to organic and inorganic acid and approximately 40% is protein-bound (primarily to ablumin).

Elimination

Studies have shown a relationship between urinary calcium excretion and the intravenous administration of calcium gluconate, with a significant increase in urinary calcium excretion observed after the intravenous administration of calcium gluconate.

13 NONCLINICAL TOXICOLOGY

13.1 Carcinogenesis, Mutagenesis, Impairment of Fertility

Long-term studies in animals have not been conducted to evaluate the carcinogenic potential of Calcium Gluconate Injection. Calcium gluconate was not mutagenic with or without metabolic activation in the Ames test with Salmonella typhimurium (strains TA-1535, TA-1537, and TA-1538) or Saccharomyces cerevisiae (Strain D4). Fertility studies in animals have not been conducted with calcium gluconate administered by the intravenous route.

HOW SUPPLIED/STORAGE AND HANDLING

Calcium Gluconate Injection, USP is a clear, colorless to slightly yellow solution supplied as follows:

Store at 20° to 25°C (68° to 77°F) [see USP Controlled Room Temperature]. Do not freeze.

Preservative Free. Discard any unused portion in the single-dose vial immediately or the Pharmacy Bulk Package vial within 4 hours after initial closure puncture.

Each dose dispensed from the Pharmacy Bulk Package vial must be used immediately.

The diluted solution must be used immediately.

NOTE: Supersaturated solutions are prone to precipitation. The precipitate, if present, may be dissolved by warming the vial to 60° to 80°C, with occasional agitation, until the solution becomes clear. Shake vigorously. Allow to cool to room temperature before dispensing. Use injection only if clear immediately prior to use.

Product repackaged by: Henry Schein, Inc., Bastian, VA 24314
From Original Manufacturer/Distributor's NDC and Unit of Sale | To Henry Schein Repackaged Product NDC and Unit of Sale | Total Strength/Total Volume (Concentration) per unit
NDC 63323-360-19 25 x 10 mL single dose vials | NDC 0404-9831-10 1 10 mL single dose vial in a bag (Vial bears NDC 63323-360-01) | 1,000 mg calcium gluconate per 10 mL (100 mg per mL)
NDC 63323-360-59 25 x 50 mL single dose vials | NDC 0404-9831-50 1 50 mL single dose vial in a bag (Vial bears NDC 63323-360-03) | 5,000 mg calcium gluconate per 50 mL (100 mg per mL)

PATIENT COUNSELING INFORMATION

- Advise the patient that the risks associated with infusion including local tissue inflammation, local necrosis and calcinosis. [see Warnings and Precautions (5.3)] .

FRESENIUS KABI

Lake Zurich, IL 60047

www.fresenius-kabi.com/us

451463C

Revised: June 2023